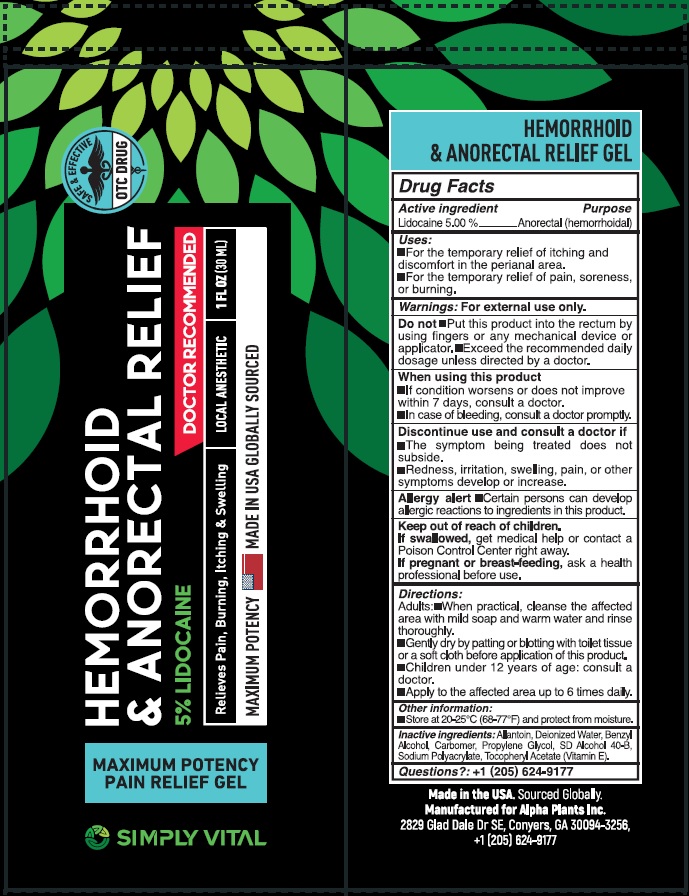 DRUG LABEL: SIMPLY VITAL HEMORRHOID and ANORECTAL RELIEF
NDC: 82460-262 | Form: CREAM
Manufacturer: ALPHA PLANTS INC
Category: otc | Type: HUMAN OTC DRUG LABEL
Date: 20231111

ACTIVE INGREDIENTS: LIDOCAINE 50 mg/1 mL
INACTIVE INGREDIENTS: ALLANTOIN; WATER; BENZYL ALCOHOL; CARBOMER HOMOPOLYMER, UNSPECIFIED TYPE; PROPYLENE GLYCOL; .ALPHA.-TOCOPHEROL ACETATE

SIMPLY VITAL HEMORRHOID & ANORECTAL RELIEF

Active ingredient

Lidocaine 5.00 %

Purpose

Anorectal (hemorrhoidal)

Uses:

- For the temporary relief of itching and discomfort in the perianal area.
- For the temporary relief of pain, soreness, or burning.

Warnings:

For external use only.

Do not

- Put this product into the rectum by using fingers or any mechanical device or applicator.
- Exceed the recommended daily dosage unless directed by a doctor.

When using this product

- If condition worsens or does not improve within 7 days, consult a doctor.
- In case of bleeding, consult a doctor promptly.

Discontinue use and consult a doctor if

- The symptoms being treated does not subside.
- Redness, irritation, swelling, pain, or other symptoms develop or increase.

- Certain persions can develop allergic reactions to ingredients in this product.

Allergy alert

Keep out of reach of children.

get medical help or contact a Poison Control Center right away. If swallowed,

If pregnant or breast-feeding,

ask a health professional before use.

Directions:

Adults:• When practical, cleanse the affected area with mild soap and warm water and rinse thoroughly.

• Gently dry by patting or blotting with toilet tissue or a soft cloth before application of this product.

• Children under 12 years of age: consult a doctor.

• Apply to the affected area up to 6 times daily.

Other information:

- Store at 20-25°C (68-77°F) and protect from moisture.

Inactive ingredients:

Allantoin, Deionized Water, Benzyl Alcohol, Carbomer, Propylene Glycol, SD Alcohol 40-B, Sodium Polyacrylate, Tocopheryl Acetate (Vitamin E).

Questions?

+1 (205) 624-9177